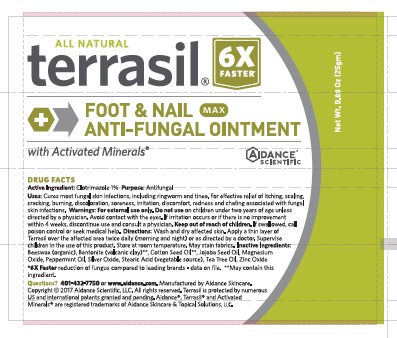 DRUG LABEL: Terrasil Foot and Nail Anti-Fungal
NDC: 24909-126 | Form: OINTMENT
Manufacturer: Aidance Skincare & Topical Solutions, LLC
Category: otc | Type: HUMAN OTC DRUG LABEL
Date: 20181229

ACTIVE INGREDIENTS: CLOTRIMAZOLE 1.0 g/100 g
INACTIVE INGREDIENTS: BENTONITE; COTTONSEED OIL; JOJOBA OIL; MAGNESIUM OXIDE; PEPPERMINT OIL; SILVER OXIDE; STEARIC ACID; TEA TREE OIL; WHITE WAX; ZINC OXIDE

Drug Facts

Active Ingredient

Clotrimazole 1%

Purpose

Antifungal

Uses

Cures most fungal skin infections, including ringworm and tinea. For effective relief of itching,
scaling, cracking, burning, discoloration, soreness, irritation, discomfort, redness and chafing
associated with fungal skin infections.

Warnings

For external use only. Do not use on children under two years of age unless directed by
a physician. Avoid contact with the eyes. If irritation occurs or if there is no improvement within 4
weeks, discontinue use and consult a physician.

Directions

Wash and dry affected skin. Apply a thin layer of cream over the affected area
twice daily (morning and night) or as directed by a doctor. Supervise children in the use of
this product. Store at room temperature. May stain fabrics.

Inactive Ingredients

beeswax (organic), cotton seed oil, bentonite (volcanic clay), jojoba seed oil, magnesium oxide, peppermint oil, silver oxide, stearic acid, tea tree oil, zinc oxide.

Questions?401-432-7750 or www.Aidance.com

PRINCIPAL DISPLAY PANEL - 25g Tube

ALL NATURAL

terrasil

MAX Strength

FOOT & NAIL

ANTI-FUNGAL OINTMENT

with Activated Minerals®